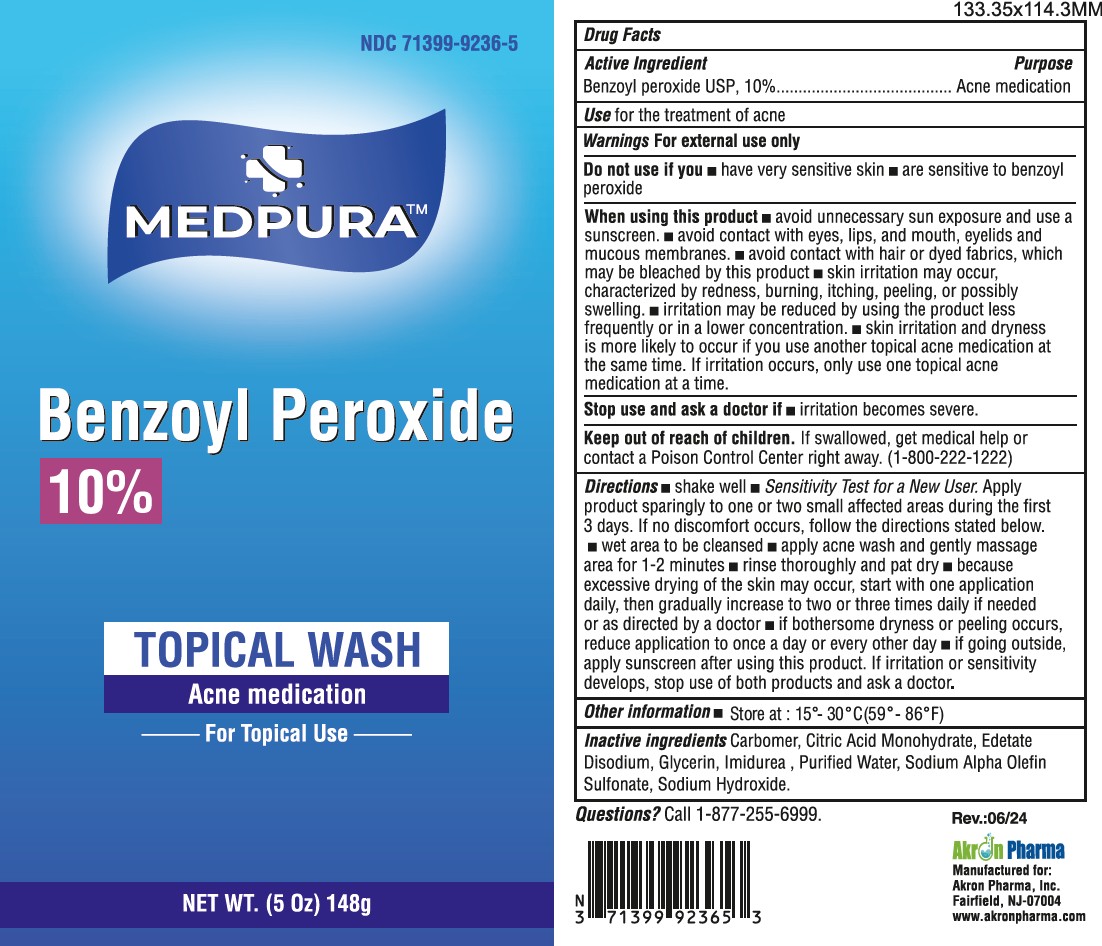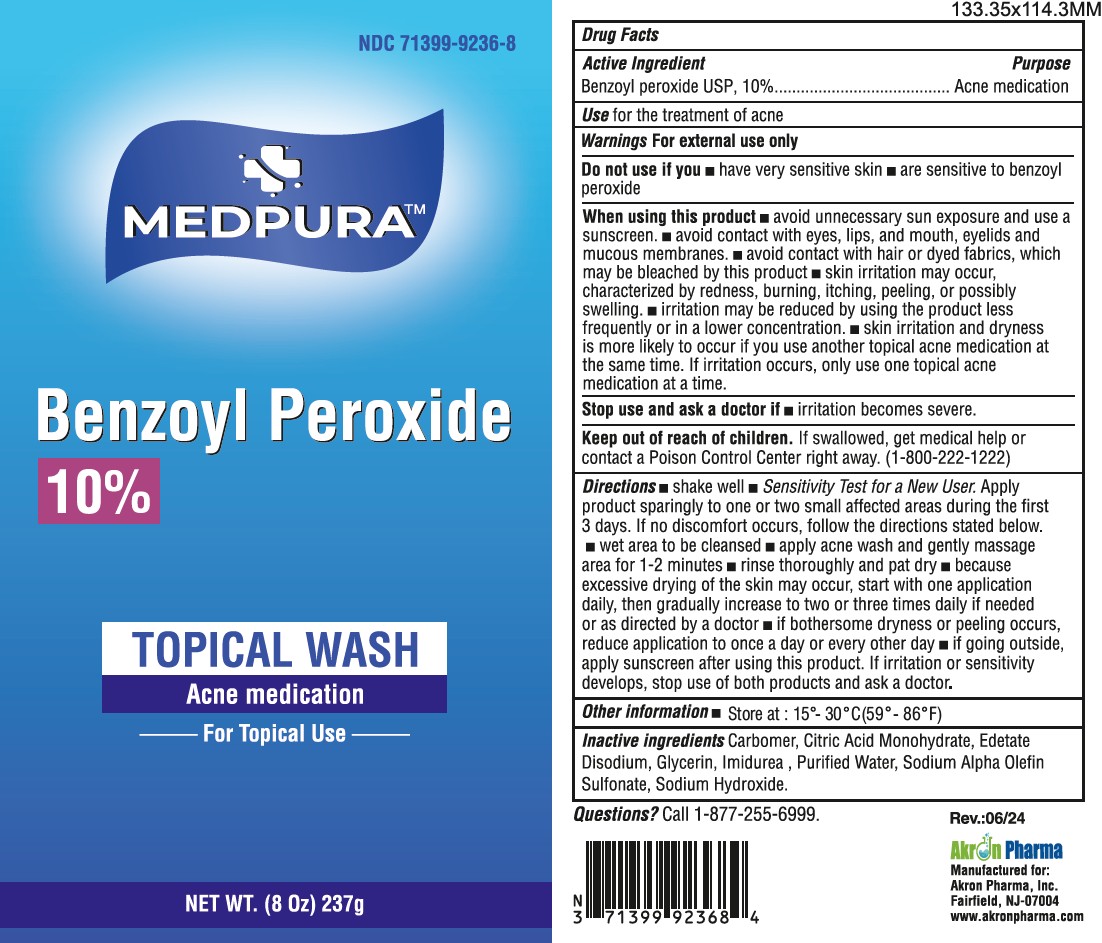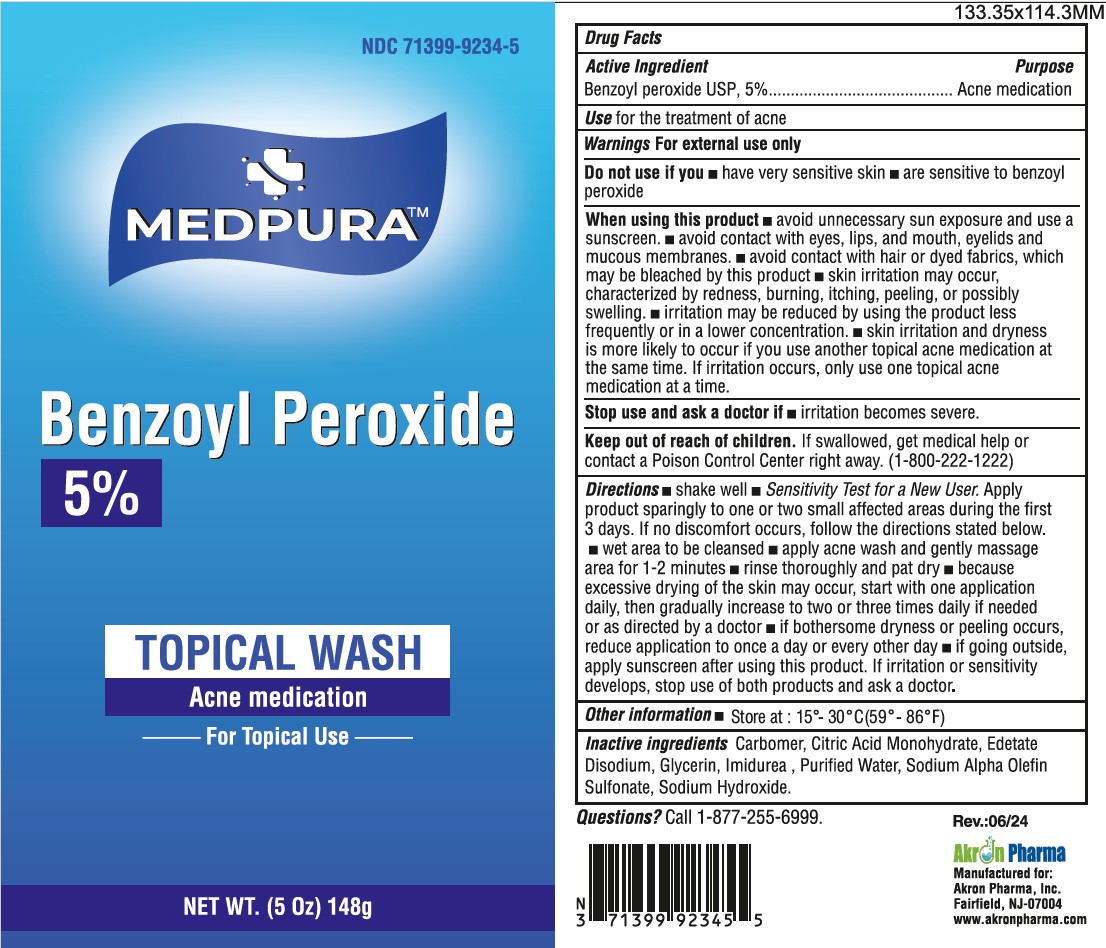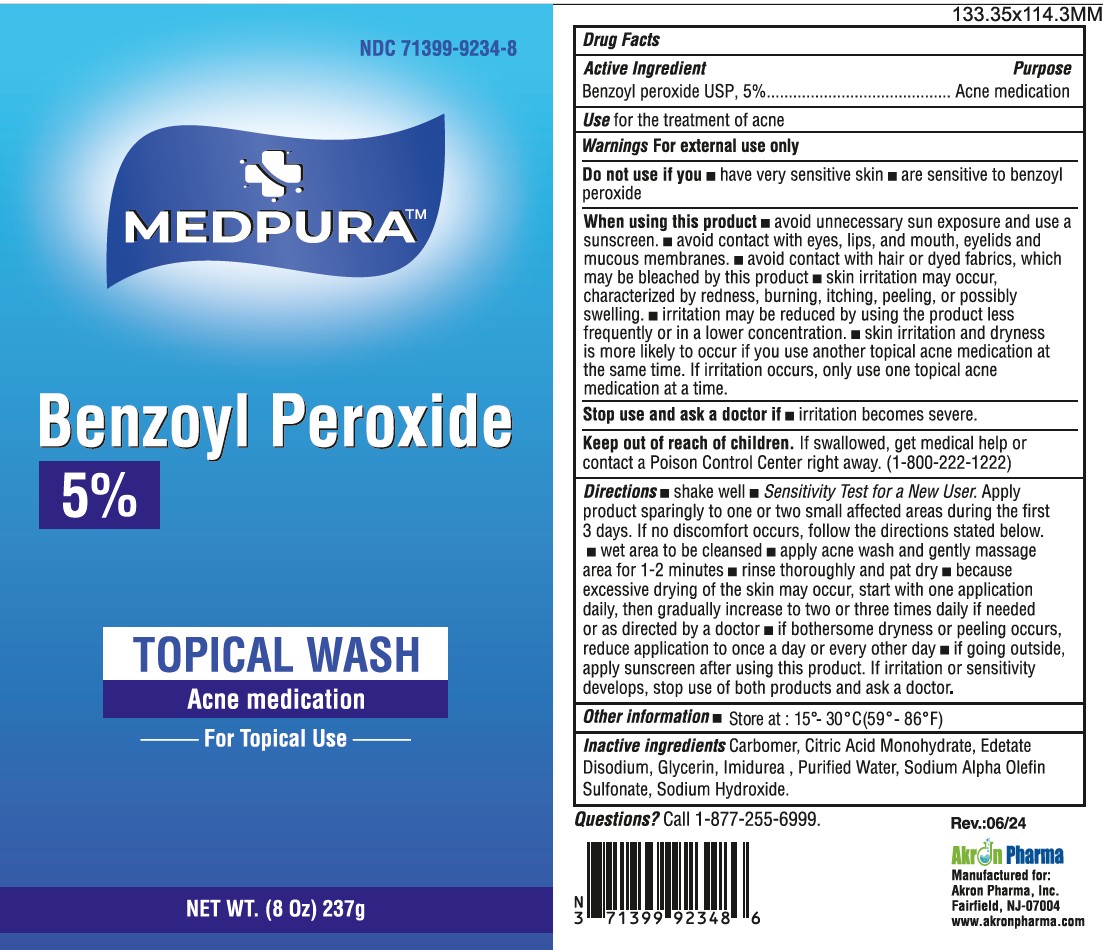 DRUG LABEL: MEDPURA Benzoyl Peroxide
NDC: 71399-9234 | Form: LIQUID
Manufacturer: Akron Pharma Inc.
Category: otc | Type: HUMAN OTC DRUG LABEL
Date: 20260113

ACTIVE INGREDIENTS: BENZOYL PEROXIDE 50 mg/1 mL
INACTIVE INGREDIENTS: CARBOMER 980; CITRIC ACID MONOHYDRATE; EDETATE DISODIUM; GLYCERIN; IMIDUREA; SODIUM C14-16 OLEFIN SULFONATE; SODIUM HYDROXIDE; WATER

MEDPURA 5% and 10% Benzoyl Peroxide
Acne Treatment Wash

Drug Facts

Active ingredient

Benzoyl peroxide 5%

Benzoyl peroxide 10%

Purpose

Acne treatment

Use

for the treatment of acne

Warnings

For external use only

Do not use this medication if you have very sensitive skin or if you are sensitive to benzoyl peroxide.

When using this product

- avoid unnecessary sun exposure and use a sunscreen.
- avoid contact with eyes, lips, and mouth, eyelids and mucous membranes.
- avoid contact with hair or dyed fabrics, which may be bleached by this product
- skin irritation may occur, characterized by redness, burning, itching, peeling, or possibly swelling.
- irritation may be reduced by using the product less frequently or in a lower concentration.
- skin irritation and dryness is more likely to occur if you use another topical acne medication at the same time. If irritation occurs, only use one topical acne medication at a time.

Keep out of reach of children. If swallowed, get medical help or contact a Poison Control Center right away. (1-800-222-1222)

Directions

- Shake well
- Sensitivity Test for a New User. Apply product sparingly to one or two small affected areas during the first 3 days. If no discomfort occurs, follow the directions stated below.
- wet area to be cleansed
- apply acne wash and gently massage area for 1-2 minutes
- rinse thoroughly and pat dry
- because excessive drying of the skin may occur, start with one application daily, then gradually increase to two or three times daily if needed or as directed by a doctor
- if bothersome dryness or peeling occurs, reduce application to once a day or every other day
- if going outside, apply sunscreen after using this product. If irritation or sensitivity develops, stop use of both products and ask a doctor.

Other information

store at controlled room temperature, 15°- 30°C (59°- 86°F)

Inactive ingredients

Benzoyl peroxide, Carbomer, Citric acid monohydrate, Edetate Disodium, Glycerin,Imidurea, Sodium alpha olefin sulfonate,

Sodium hydroxide, Purified water.

Questions or comments?

call toll-free 1-877-225-6999

Manufactured for:

Akron Pharma, Inc.
Fairfield, NJ-07004
www.akronpharma.com